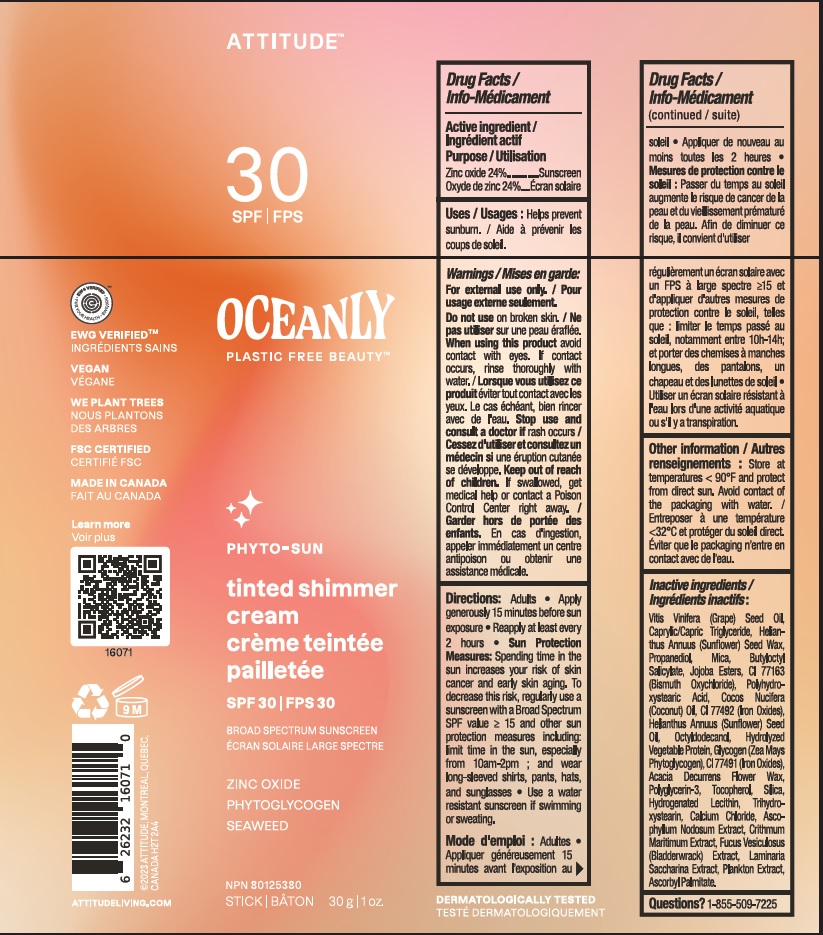 DRUG LABEL: ATTITUDE Oceanly Phyto-Sun Tinted Shimmer Cream SPF 30
NDC: 61649-071 | Form: STICK
Manufacturer: 9055-7588 Quebec Inc. DBA Attitude
Category: otc | Type: HUMAN OTC DRUG LABEL
Date: 20251020

ACTIVE INGREDIENTS: ZINC OXIDE 24 g/100 g
INACTIVE INGREDIENTS: SUNFLOWER OIL; HYDROGENATED SOYBEAN LECITHIN; SILICON DIOXIDE; MEDIUM-CHAIN TRIGLYCERIDES; FERRIC OXIDE YELLOW; COCONUT OIL; ACACIA DECURRENS FLOWER WAX; POLYGLYCERIN-3; .ALPHA.-TOCOPHEROL; TRIHYDROXYSTEARIN; FUCUS VESICULOSUS; GLYCOGEN; BUTYLOCTYL SALICYLATE; POLYHYDROXYSTEARIC ACID (2300 MW); OCTYLDODECANOL; FERRIC OXIDE RED; CRITHMUM MARITIMUM; CORN; ASCORBYL PALMITATE; HYDROLYZED WHEAT PROTEIN (ENZYMATIC, 3000 MW); HYDROLYZED SOY PROTEIN (ENZYMATIC; 2000 MW); ASCOPHYLLUM NODOSUM; PROPANEDIOL; BISMUTH OXYCHLORIDE; CALCIUM CHLORIDE; SACCHARINA LATISSIMA; JOJOBA OIL; GRAPE SEED OIL; HELIANTHUS ANNUUS SEED WAX; MICA; TETRASELMIS SUECICA

ATTITUDE Oceanly Phyto-Sun Tinted Shimmer Cream - SPF 30

DRUG FACTS

ACTIVE INGREDIENT

Zinc oxide (24 %)

PURPOSE

Sunscreen

INDICATIONS AND USAGE

Helps prevent sunburn.

WARNINGS

For external use only.

Do not use on broken skin.

When using this product avoid contact with eyes. If contact occurs, rinse thoroughly with water.

Keep out of reach of children. If swallowed, get medical help or contact a Poison Control Center right away.

Stop use and consult a doctor if rash occurs.

DOSAGE AND ADMINISTRATION

Adults.

- Apply generously 15 minutes before sun exposure.
- Reapply at least every 2 hours.
- Sun Protection Measures: Spending time in the sun increases your risk of skin cancer and early aging. To decrease this risk, regularly use a sunscreen with a Broad Spectrum SPFvalue of 15 or higher and other sun protection measures including: limit time in the sun, especially from 10am-2pm; and wear long-sleeved shirts, pants, hats and sunglasses.
- Use a water resistant sunscreen if swimming or sweating.

INACTIVE INGREDIENT

Vitis Vinifera (Grape) Seed Oil, Caprylic/Capric Triglyceride, Helianthus Annuus (Sunflower) Seed Wax, Propanediol, Mica, Butyloctyl Salicylate, Jojoba Esters, CI 77163 (Bismuth Oxychloride), Polyhydroxystearic Acid, Cocos Nucifera (Coconut) Oil, CI 77492 (Iron Oxides), Helianthus Annuus (Sunflower) Seed Oil, Octyldodecanol, Hydrolyzed Vegetable Protein, Glycogen (Zea Mays Phytoglycogen), CI 77491 (Iron Oxides), Acacia Decurrens Flower Wax, Polyglycerin-3, Tocopherol, Silica, Hydrogenated Lecithin, Trihydroxystearin, Calcium Chloride, Ascophyllum Nodosum Extract, Crithmum Maritimum Extract, Fucus Vesiculosus (Bladderwrack) Extract, Laminaria Saccharina Extract, Plankton Extract, Ascorbyl Palmitate.

STORAGE AND HANDLING

Store at temperatures < 90F and protect from direct sun. Avoid contact of packaging with water.

Questions ? 1-855-509-7225

PACKAGE LABEL

ATTITUDETM

SPF 30

OCEANLY PLASTIC FREE BEAUTYTM

PHYTO-SUN

Tinted shimmer cream

Broad spectrum sunscreen

Zinc oxide

Phytoglycogen

Seaweed

NPN 80125380

Stick 30 g / 1 oz.

EWG Verified

Vegan

We plant trees

FSC Certified

Made in Canada

Dermatologically tested